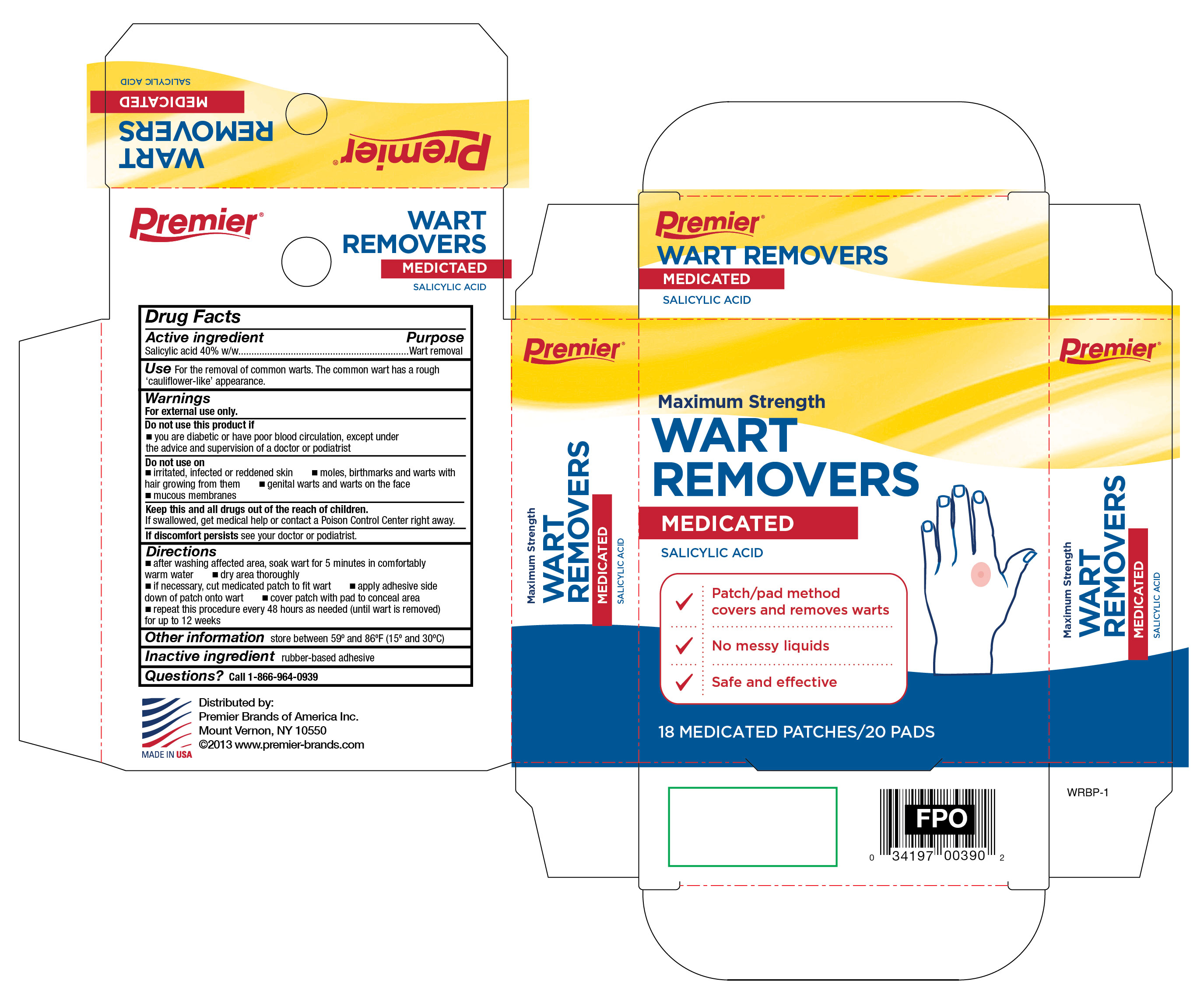 DRUG LABEL: Salicylic Acid
NDC: 56104-017 | Form: PATCH
Manufacturer: Premier Brands of America Inc.
Category: otc | Type: HUMAN OTC DRUG LABEL
Date: 20260109

ACTIVE INGREDIENTS: SALICYLIC ACID 40 mg/18 1
INACTIVE INGREDIENTS: POLYVINYL ALCOHOL; HIGH DENSITY POLYETHYLENE

Premier Brands Wart Removers

Active ingredient

Salicylic acid

Purpose

Wart removal

Use

For the removal of common warts. The common wart has a rough 'cauliflower-like' appearance.

Warnings

For external use only.

Do not use this product if

- you are a diabetic or have poor blood circulation, except under the advice and supervision of a doctor or podiatrist

Do not use on

- irritated, infected or reddened skin
- moles, birthmarks and warts with hair growing from them
- genital warts and warts on face
- mucous membranes

Keep out of reach of children

If swallowed, get medical help or contact a Poison Control Center right away.

Stop and ask a doctor

If discomfort persists see your doctor or podiatrist

Directions

- after washing affected area, soak wart for 5 minutes in comfortably warm water
- dry area thoroughly
- if necessary, cut medicated patch to fit wart
- apply adhesive side down of patch onto wart
- cover patch with pad to conceal area
- repeat this procedure every 48 hours as needed (until wart is removed) for up to 12 weeks

Other information

store between 59°F to 86°F (15°C to 30°C)

Inactive ingredients

rubber-based adhesive

Questions?

call 1-866-964-0939

RECENT MAJOR CHANGES

..

Principal Display Panel

Premier

Maximum Strength

Wart Removers
Medicated
Salicylic Acid

- Patch/Pad method covers and removes wart
- No messy liquids
- Safe and effective

18 Medicated Patches/20 Pads